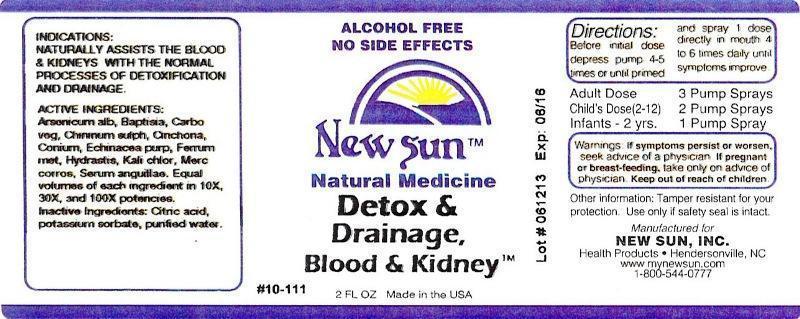 DRUG LABEL: Detox and Drainage, Blood and Kidney
NDC: 66579-0013 | Form: LIQUID
Manufacturer: New Sun Inc.
Category: homeopathic | Type: HUMAN OTC DRUG LABEL
Date: 20140905

ACTIVE INGREDIENTS: ARSENIC TRIOXIDE 10 [hp_X]/59 mL; BAPTISIA TINCTORIA ROOT 10 [hp_X]/59 mL; ACTIVATED CHARCOAL 10 [hp_X]/59 mL; QUININE SULFATE 10 [hp_X]/59 mL; CINCHONA OFFICINALIS BARK 10 [hp_X]/59 mL; CONIUM MACULATUM FLOWERING TOP 10 [hp_X]/59 mL; ECHINACEA PURPUREA 10 [hp_X]/59 mL; IRON 10 [hp_X]/59 mL; GOLDENSEAL 10 [hp_X]/59 mL; POTASSIUM CHLORATE 10 [hp_X]/59 mL; MERCURIC CHLORIDE 10 [hp_X]/59 mL; ANGUILLA ROSTRATA BLOOD SERUM 10 [hp_X]/59 mL
INACTIVE INGREDIENTS: CITRIC ACID MONOHYDRATE; POTASSIUM SORBATE; WATER

Detox and Drainage, Blood and Kidney

DOSAGE AND ADMINISTRATION

Directions: Before initial dose depress pump 4-5 times or until primed and spray 1 dose directly in mouth 4 to 6 times daily until symptoms improve.

Adult Dose: 3 Pump Sprays

Child's Dose (2-12): 2 Pump Sprays

Infants - 2 yrs: 1 Pump Spray

WARNINGS

Warnings: If symptoms persist or worsen, seek advice of physician. If pregnant or breast-feeding, take only on advice of a physician.

Keep out of reach of children.

Other information: Tamper resistant for your protection. Use only if safety seal is intact.

PURPOSE

Indications: Naturally assists the blood and kidneys with the normal processes of detoxification and drainage.

ACTIVE INGREDIENT

Active Ingredients: Arsenicum album, Baptisia tinctoria, Carbo vegetabilis, Chininum sulphuricum, Cinchona officinalis, Conium maculatum, Echinacea purpurea, Ferrum metallicum, Hydrastis canadensis, Kali chloricum, Mercurius corrosivus, Serum anguillae. Equal volumes of each ingredient in 10X, 30X, 100X potencies.

Inactive Ingredient: Citric acid, potassium sorbate, purified water.

INDICATIONS AND USAGE

Indications: Naturally assists the blood and kidneys with the normal processes of detoxification and drainage.